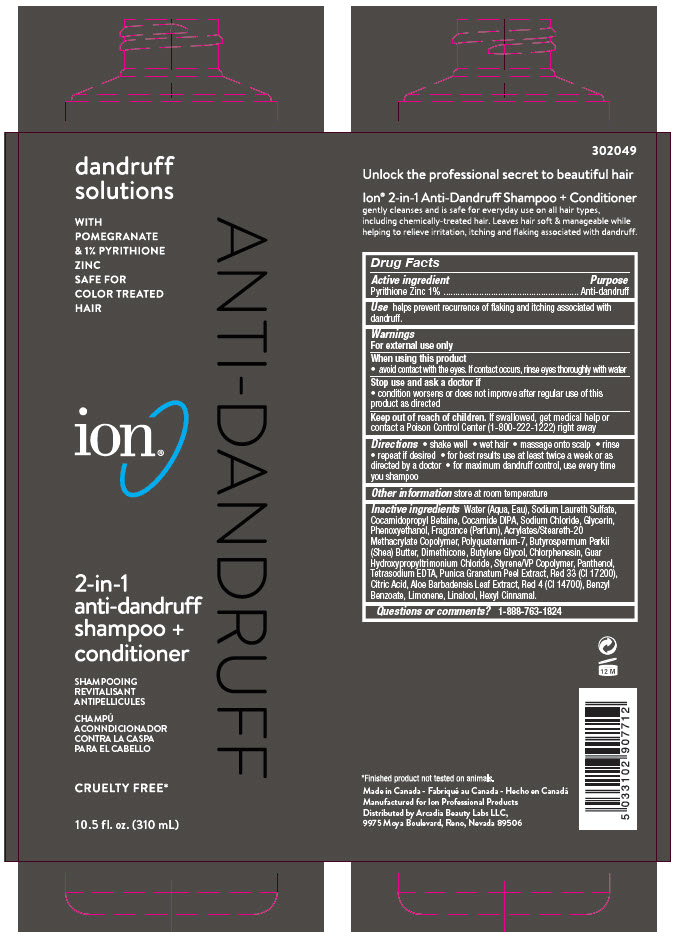 DRUG LABEL: ion 2 in 1 anti-dandruff
NDC: 71990-712 | Form: SHAMPOO
Manufacturer: Arcadia Beauty Labs LLC
Category: otc | Type: HUMAN OTC DRUG LABEL
Date: 20240828

ACTIVE INGREDIENTS: PYRITHIONE ZINC 10 mg/1 mL
INACTIVE INGREDIENTS: Water; SODIUM LAURETH-3 SULFATE; Cocamidopropyl Betaine; COCO DIISOPROPANOLAMIDE; Sodium Chloride; Glycerin; Phenoxyethanol; ETHYL ACRYLATE/METHACRYLIC ACID/STEARETH-20 METHACRYLATE COPOLYMER; POLYQUATERNIUM-7 (70/30 ACRYLAMIDE/DADMAC; 1600000 MW); SHEA BUTTER; Dimethicone; Butylene Glycol; Chlorphenesin; Guar Hydroxypropyltrimonium Chloride; Panthenol; EDETATE SODIUM; D&C RED NO. 33; CITRIC ACID MONOHYDRATE; ALOE VERA LEAF; FD&C RED NO. 4; Benzyl Benzoate; LIMONENE, (+)-; LINALOOL, (+/-)-; .ALPHA.-HEXYLCINNAMALDEHYDE

ion® 2 in 1 anti-dandruff shampoo + conditioner
Anti-dandruff

Drug Facts

Active ingredient

Pyrithione Zinc 1%

Purpose

Anti-dandruff

Use

helps prevent recurrence of flaking and itching associated with dandruff.

Warnings

For external use only

When using this product

- avoid contact with the eyes. If contact occurs, rinse eyes thoroughly with water

Stop use and ask a doctor if

- condition worsens or does not improve after regular use of this product as directed

Keep out of reach of children. If swallowed, get medical help or contact a Poison Control Center (1-800-222-1222) right away

Directions

- shake well
- wet hair
- massage onto scalp
- rinse
- repeat if desired
- for best results use at least twice a week or as directed by a doctor
- for maximum dandruff control, use every time you shampoo

Other information

store at room temperature

Inactive ingredients

Water (Aqua, Eau), Sodium Laureth Sulfate, Cocamidopropyl Betaine, Cocamide DIPA, Sodium Chloride, Glycerin, Phenoxyethanol, Fragrance (Parfum), Acrylates/Steareth-20 Methacrylate Copolymer, Polyquaternium-7, Butyrospermum Parkii (Shea) Butter, Dimethicone, Butylene Glycol, Chlorphenesin, Guar Hydroxypropyltrimonium Chloride, Styrene/VP Copolymer, Panthenol, Tetrasodium EDTA, Punica Granatum Peel Extract, Red 33 (CI 17200), Citric Acid, Aloe Barbadensis Leaf Extract, Red 4 (CI 14700), Benzyl Benzoate, Limonene, Linalool, Hexyl Cinnamal.

Questions or comments?

1-888-763-1824

Distributed by Arcadia Beauty Labs LLC,
9975 Moya Boulevard, Reno, Nevada 89506

PRINCIPAL DISPLAY PANEL - 310 mL Bottle Carton

dandruff
solutions

WITH
POMEGRANATE
& 1% PYRITHIONE
ZINC
SAFE FOR
COLOR TREATED
HAIR

ion®

2-in-1
anti-dandruff
shampoo +
conditioner

SHAMPOOING
REVITALISANT
ANTIPELLICULES

CRUELTY FREE*

10.5 fl. oz. (310 mL)

ANTI-DANDRUFF